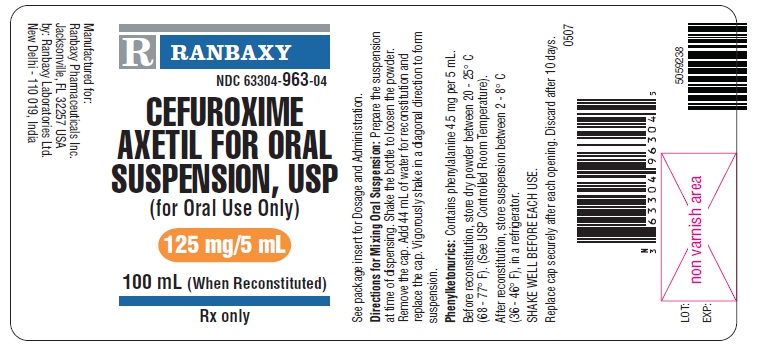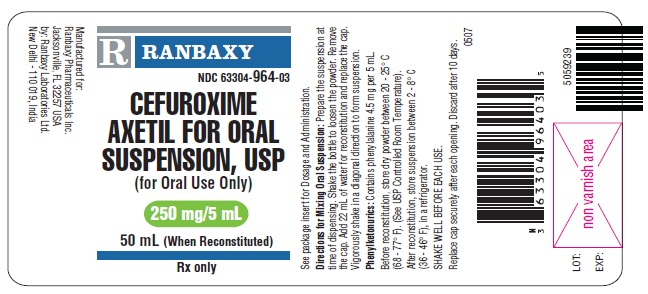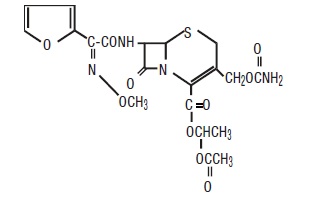 DRUG LABEL: Cefuroxime Axetil For Oral Suspension
NDC: 63304-963 | Form: SUSPENSION
Manufacturer: Ranbaxy Pharmaceuticals Inc
Category: prescription | Type: HUMAN PRESCRIPTION DRUG LABEL
Date: 20130819

ACTIVE INGREDIENTS: CEFUROXIME AXETIL 125 mg/5 mL
INACTIVE INGREDIENTS: ASPARTAME; HYPROMELLOSE PHTHALATE (24% PHTHALATE, 55 CST); MANNITOL; METHACRYLIC ACID - METHYL METHACRYLATE COPOLYMER (1:1); MONOSODIUM CITRATE; SILICON DIOXIDE; SODIUM BENZOATE; SODIUM CHLORIDE; SUCROSE; XANTHAN GUM

CEFUROXIME AXETIL FOR ORAL SUSPENSION,USP
Rx Only

To reduce the development of drug-resistant bacteria and maintain the effectiveness of cefuroxime axetil for oral suspension and other antibacterial drugs, cefuroxime axetil for oral suspension should be used only to treat or prevent infections that are proven or strongly suspected to be caused by bacteria.

DESCRIPTION

Cefuroxime axetil for oral suspension, USP contains cefuroxime as cefuroxime axetil. Cefuroxime axetil USP is a semisynthetic, broad-spectrum cephalosporin antibiotic for oral administration.

Chemically, cefuroxime axetil, the 1-(acetyloxy) ethyl ester of cefuroxime, is (RS)-1- hydroxyethyl (6R,7R)-7-[2-(2-furyl)glyoxylamido]-3-(hydroxymethyl)-8-oxo-5-thia-1- azabicyclo[4.2.0]oct-2-ene-2-carboxylate, 7^2-(Z)-(O-methyl-oxime), 1-acetate 3-carbamate. Its molecular formula is C20H22N4O10S, and it has a molecular weight of 510.48.

Cefuroxime axetil is in the crystalline form and has the following structural formula:

Cefuroxime axetil for oral suspension USP, when reconstituted with water, provides the equivalent of 125 mg or 250 mg of cefuroxime (as cefuroxime axetil) per 5 mL of suspension. Cefuroxime axetil USP for oral suspension contains the following inactive ingredients: aspartame, hypromellose phthalate, mannitol, methacrylic acid copolymer, monosodium citrate, peppermint flavor, silicon dioxide, sodium benzoate, sodium chloride, sucrose, tutti frutti flavor, xanthan gum.

CLINICAL PHARMACOLOGY

Absorption and Metabolism: After oral administration, cefuroxime axetil is absorbed from the gastrointestinal tract and rapidly hydrolyzed by nonspecific esterases in the intestinal mucosa and blood to cefuroxime. Cefuroxime is subsequently distributed throughout the extracellular fluids. The axetil moiety is metabolized to acetaldehyde and acetic acid.

Pharmacokinetics: Approximately 50% of serum cefuroxime is bound to protein. Serum pharmacokinetic parameters for cefuroxime axetil for oral suspension are shown in Table 1.

Table 1. Postprandial Pharmacokinetics of Cefuroxime Administered as Cefuroxime Axetil for Oral Suspension to Pediatric Patients*
Dose† (Cefuroxime Equivalent) | n | Peak Plasma Concentration (mcg/mL) | Time of Peak Plasma Concentration (hr) | Mean Elimination Half-Life (hr) | AUC (mcg-hr mL)
10 mg/kg | 8 | 3.3 | 3.6 | 1.4 | 12.4
15 mg/kg | 12 | 5.1 | 2.7 | 1.9 | 22.5
20 mg/kg | 8 | 7 | 3.1 | 1.9 | 32.8

*Mean age = 23 months.

†Drug administered with milk or milk products

Comparative Pharmacokinetic Properties: A 250 mg/5 mL dose of cefuroxime axetil for oral suspension is bioequivalent to 2 times 125 mg/5 mL dose of cefuroxime axetil for oral suspension when administered with food (see Table 2). Cefuroxime axetil for oral suspension was not bioequivalent to cefuroxime axetil tablets when tested in healthy adults. The tablet and powder for oral suspension formulations are NOT substitutable on a milligram-per-milligram basis. The area under the curve for the suspension averaged 91% of that for the tablet, and the peak plasma concentration for the suspension averaged 71% of the peak plasma concentration of the tablets. Therefore, the safety and effectiveness of both the tablet and oral suspension formulations had to be established in separate clinical trials.

Table 2: Pharmacokinetics of Cefuroxime Administered as 250 mg/5 mL or 2 x 125 mg/5 mL Cefuroxime Axetil for Oral Suspension to Adults* With Food
Dose (Cefuroxime Equivalent) | Peak Plasma Concentration (mcg/mL) | Time of Peak Plasma Concentration (hr) | Mean Elimination Half-Life (hr) | AUC (mcg-hr mL)
250 mg/5 mL | 2.23 | 3 | 1.40 | 8.92
2 x 125 mg/5 mL | 2.37 | 3 | 1.44 | 9.75

*Mean values of 18 healthy adult volunteers

Food Effect on Pharmacokinetics: All pharmacokinetic and clinical effectiveness and safety studies in pediatric patients using the suspension formulation were conducted in the fed state. No data are available on the absorption kinetics of the suspension formulation when administered to fasted pediatric patients.

Renal Excretion: Cefuroxime is excreted unchanged in the urine; in adults, approximately 50% of the administered dose is recovered in the urine within 12 hours. The pharmacokinetics of cefuroxime in the urine of pediatric patients have not been studied at this time. Until further data are available, the renal pharmacokinetic properties of cefuroxime axetil established in adults should not be extrapolated to pediatric patients.

Because cefuroxime is renally excreted, the serum half-life is prolonged in patients with reduced renal function. In a study of 20 elderly patients (mean age = 83.9 years) having a mean creatinine clearance of 34.9 mL/min, the mean serum elimination half-life was 3.5 hours. Despite the lower elimination of cefuroxime in geriatric patients, dosage adjustment based on age is not necessary (see PRECAUTIONS: Geriatric Use).

Microbiology: The in vivo bactericidal activity of cefuroxime axetil is due to cefuroxime's binding to essential target proteins and the resultant inhibition of cell-wall synthesis.

Cefuroxime has bactericidal activity against a wide range of common pathogens, including many beta-lactamase-producing strains. Cefuroxime is stable to many bacterial beta-lactamases, especially plasmid-mediated enzymes that are commonly found in enterobacteriaceae.

Cefuroxime has been demonstrated to be active against most strains of the following microorganisms both in vitro and in clinical infections as described in the INDICATIONS AND USAGE section (see INDICATIONS AND USAGE section).

Aerobic Gram-Positive Microorganisms:

Staphylococcus aureus (including beta-lactamase-producing strains)

Streptococcus pneumoniae

Streptococcus pyogenes

Aerobic Gram-Negative Microorganisms:

Escherichia coli

Haemophilus influenzae (including beta-lactamase-producing strains)

Haemophilus parainfluenzae

Klebsiella pneumoniae

Moraxella catarrhalis (including beta-lactamase-producing strains)

Neisseria gonorrhoeae (including beta-lactamase-producing strains)

Spirochetes:

Borrelia burgdorferi

Cefuroxime has been shown to be active in vitro against most strains of the following microorganisms; however, the clinical significance of these findings is unknown.

Cefuroxime exhibits in vitro minimum inhibitory concentrations (MICs) of 4 mcg/mL or less (systemic susceptible breakpoint) against most (> 90%) strains of the following microorganisms; however, the safety and effectiveness of cefuroxime in treating clinical infections due to these microorganisms have not been established in adequate and well-controlled trials.

Aerobic Gram-Positive Microorganisms:

Staphylococcus epidermidis

Staphylococcus saprophyticus

Streptococcus agalactiae

NOTE: Listeria monocytogenes and certain strains of enterococci, e.g., Enterococcus faecalis (formerly Streptococcus faecalis), are resistant to cefuroxime. Methicillin-resistant staphylococci are resistant to cefuroxime.

Aerobic Gram-Negative Microorganisms:

Morganella morganii

Proteus inconstans

Proteus mirabilis

Providencia rettgeri

NOTE: Pseudomonas spp., Campylobacter spp., Acinetobactercalcoaceticus, Legionella spp., and most strains of Serratia spp. and Proteus vulgaris are resistant to most first- and second-generation cephalosporins. Some strains of Morganellamorganii, Enterobactercloacae, and Citrobacter spp. have been shown by in vitro tests to be resistant to cefuroxime and other cephalosporins.

Anaerobic Microorganisms:

Peptococcusniger

NOTE: Most strains of Clostridium difficile and Bacteroides fragilis are resistant to cefuroxime.

Susceptibility Tests: Dilution Techniques: Quantitative methods that are used to determine MICs provide reproducible estimates of the susceptibility of bacteria to antimicrobial compounds. One such standardized procedure uses a standardized dilution method^1 (broth, agar, or microdilution) or equivalent with cefuroxime powder. The MIC values obtained should be interpreted according to the following criteria:

MIC (mcg/mL) | Interpretation
≤ 4 | (S) Susceptible
8 to16 | (I) Intermediate
≥ 32 | (R) Resistant

A report of "Susceptible" indicates that the pathogen, if in the blood, is likely to be inhibited by usually achievable concentrations of the antimicrobial compound in blood. A report of "Intermediate" indicates that inhibitory concentrations of the antibiotic may be achieved if high dosage is used or if the infection is confined to tissues or fluids in which high antibiotic concentrations are attained. This category also provides a buffer zone that prevents small, uncontrolled technical factors from causing major discrepancies in interpretation. A report of "Resistant" indicates that usually achievable concentrations of the antimicrobial compound in the blood are unlikely to be inhibitory and that other therapy should be selected.

Standardized susceptibility test procedures require the use of laboratory control microorganisms. Standard cefuroxime powder should give the following MIC values:

Microorganism | MIC (mcg/mL)
Escherichia coli ATCC 25922 | 2 to 8
Staphylococcus aureus ATCC 29213 | 0.5 to 2

Diffusion Techniques: Quantitative methods that require measurement of zone diameters provide estimates of the susceptibility of bacteria to antimicrobial compounds. One such standardized procedure^2 that has been recommended (for use with disks) to test the susceptibility of microorganisms to cefuroxime uses the 30 mcg cefuroxime disk. Interpretation involves correlation of the diameter obtained in the disk test with the MIC for cefuroxime.

Reports from the laboratory providing results of the standard single-disk susceptibility test with a 30 mcg cefuroxime disk should be interpreted according to the following criteria:

Zone Diameter (mm) | Interpretation
≥ 23 | (S) Susceptible
15 to 22 | (I) Intermediate
≤ 14 | (R) Resistant

Interpretation should be as stated above for results using dilution techniques.

As with standard dilution techniques, diffusion methods require the use of laboratory control microorganisms. The 30 mcg cefuroxime disk provides the following zone diameters in these laboratory test quality control strains:

Microorganism | Zone Diameter (mm)
Escherichia coli ATCC 25922 | 20 to 26
Staphylococcus aureus ATCC 25923 | 27 to 35

INDICATIONS AND USAGE

NOTE: CEFUROXIME AXETIL TABLETS AND CEFUROXIME AXETIL FOR ORAL SUSPENSION ARE NOT BIOEQUIVALENT AND ARE NOT SUBSTITUTABLE ON AMILLIGRAM-PER-MILLIGRAM BASIS (SEE CLINICAL PHARMACOLOGY).

Cefuroxime axetil for oral suspension is indicated for the treatment of pediatric patients 3 months to 12 years of age with mild to moderate infections caused by susceptible strains of the designated microorganisms in the conditions listed below. The safety and effectiveness of cefuroxime axetil for oral suspension in the treatment of infections other than those specifically listed below have not been established either by adequate and well-controlled trials or by pharmacokinetic data with which to determine an effective and safe dosing regimen.

1. Pharyngitis/Tonsillitis caused by Streptococcus pyogenes. NOTE: The usual drug of choice in the treatment and prevention of streptococcal infections, including the prophylaxis of rheumatic fever, is penicillin given by the intramuscular route. Cefuroxime axetil for oral suspension is generally effective in the eradication of streptococci from the nasopharynx; however, substantial data establishing the efficacy of cefuroxime in the subsequent prevention of rheumatic fever are not available. Please also note that in all clinical trials, all isolates had to be sensitive to both penicillin and cefuroxime. There are no data from adequate and well-controlled trials to demonstrate the effectiveness of cefuroxime in the treatment of penicillin-resistant strains of Streptococcus pyogenes.
2. Acute Bacterial Otitis Media caused by Streptococcus pneumoniae, Haemophilus influenzae (including beta-lactamase-producing strains), Moraxella catarrhalis (including beta-lactamase-producing strains), or Streptococcus pyogenes.
3. Impetigo caused by Staphylococcus aureus (including beta-lactamase-producing strains) or Streptococcus pyogenes.

To reduce the development of drug-resistant bacteria and maintain the effectiveness of cefuroxime axetil for oral suspension and other antibacterial drugs, cefuroxime axetil for oral suspension should be used only to treat or prevent infections that are proven or strongly suspected to be caused by susceptible bacteria. When culture and susceptibility information are available, they should be considered in selecting or modifying antibacterial therapy. In the absence of such data, local epidemiology and susceptibility patterns may contribute to the empiric selection of therapy.

CONTRAINDICATIONS

Cefuroxime axetil products are contraindicated in patients with known allergy to the cephalosporin group of antibiotics.

WARNINGS

CEFUROXIME AXETIL TABLETS AND CEFUROXIME AXETIL FOR ORAL SUSPENSION ARE NOT BIOEQUIVALENT AND ARE THEREFORE NOT SUBSTITUTABLE ON A MILLIGRAM-PER-MILLIGRAM BASIS (SEE CLINICAL PHARMACOLOGY).

BEFORE THERAPY WITH CEFUROXIME AXETIL PRODUCTS IS INSTITUTED, CAREFUL INQUIRY SHOULD BE MADE TO DETERMINE WHETHER THE PATIENT HAS HAD PREVIOUS HYPERSENSITIVITY REACTIONS TO CEFUROXIME AXETIL PRODUCTS, OTHER CEPHALOSPORINS, PENICILLINS, OR OTHER DRUGS. IF THIS PRODUCT IS TO BE GIVEN TO PENICILLIN-SENSITIVE PATIENTS, CAUTION SHOULD BE EXERCISED BECAUSE CROSS-HYPERSENSITIVITY AMONG BETA-LACTAM ANTIBIOTICS HAS BEEN CLEARLY DOCUMENTED AND MAY OCCUR IN UP TO 10% OF PATIENTS WITH A HISTORY OF PENICILLIN ALLERGY. IF A CLINICALLY SIGNIFICANT ALLERGIC REACTION TO CEFUROXIME AXETIL PRODUCTS OCCURS, DISCONTINUE THE DRUG AND INSTITUTE APPROPRIATE THERAPY. SERIOUS ACUTE HYPERSENSITIVITY REACTIONS MAY REQUIRE TREATMENT WITH EPINEPHRINE AND OTHER EMERGENCY MEASURES, INCLUDING OXYGEN, INTRAVENOUS FLUIDS, INTRAVENOUS ANTIHISTAMINES, CORTICOSTEROIDS, PRESSOR AMINES, AND AIRWAY MANAGEMENT, AS CLINICALLY INDICATED.

Clostridium difficile associated diarrhea (CDAD) has been reported with use of nearly all antibacterial agents, including cefuroxime axetil for oral suspension, and may range in severity from mild diarrhea to fatal colitis. Treatment with antibacterial agents alters the normal flora of the colon leading to overgrowth of C. difficile.

C. difficile produces toxins A and B which contribute to the development of CDAD. Hypertoxin producing strains of C. difficile cause increased morbidity and mortality, as these infections can be refractory to antimicrobial therapy and may require colectomy. CDAD must be considered in all patients who present with diarrhea following antibiotic use. Careful medical history is necessary since CDAD has been reported to occur over two months after the administration of antibacterial agents.

If CDAD is suspected or confirmed, ongoing antibiotic use not directed against C. difficile may need to be discontinued. Appropriate fluid and electrolyte management, protein supplementation, antibiotic treatment of C. difficile, and surgical evaluation should be instituted as clinically indicated.

PRECAUTIONS

General

As with other broad-spectrum antibiotics, prolonged administration of cefuroxime axetil may result in overgrowth of nonsusceptible microorganisms. If superinfection occurs during therapy, appropriate measures should be taken.

Cephalosporins, including cefuroxime axetil, should be given with caution to patients receiving concurrent treatment with potent diuretics because these diuretics are suspected of adversely affecting renal function.

Cefuroxime axetil, as with other broad-spectrum antibiotics, should be prescribed with caution in individuals with a history of colitis. The safety and effectiveness of cefuroxime axetil have not been established in patients with gastrointestinal malabsorption. Patients with gastrointestinal malabsorption were excluded from participating in clinical trials of cefuroxime axetil.

Cephalosporins may be associated with a fall in prothrombin activity. Those at risk include patients with renal or hepatic impairment, or poor nutritional state, as well as patients receiving a protracted course of antimicrobial therapy, and patients previously stabilized on anticoagulant therapy. Prothrombin time should be monitored in patients at risk and exogenous vitamin K administered as indicated.

Prescribing cefuroxime axetil for oral suspension in the absence of a proven or strongly suspected bacterial infection or a prophylactic indication is unlikely to provide benefit to the patient and increases the risk of the development of drug-resistant bacteria.

Diarrhea is a common problem caused by antibiotics which usually ends when the antibiotic is discontinued. Sometimes after starting treatment with antibiotics, patients can develop watery and bloody stools (with or without stomach cramps and fever) even as late as 2 or more months after having taken the last dose of the antibiotic. If this occurs, patients should contact their physician as soon as possible.

Information for Patients/Caregivers (Pediatric)

Phenylketonurics: Cefuroxime axetil for Oral Suspension 125 mg/5 ml and 250 mg/5 mL contain phenylalanine 4.5 mg per 5 mL (1 teaspoonful) constituted suspension.

1. During clinical trials, the tablet was tolerated by pediatric patients old enough to swallow the cefuroxime axetil tablet whole. The crushed tablet has a strong, persistent, bitter taste and should not be administered to pediatric patients in this manner. Pediatric patients who cannot swallow the tablet whole should receive the oral suspension.

2. Discontinuation of therapy due to taste and/or problems of administering this drug occurred in 1.4% of pediatric patients given the oral suspension. Complaints about taste (which may impair compliance) occurred in 5% of pediatric patients.

3. Patients should be counseled that antibacterial drugs, including cefuroxime axetil for oral suspension, should only be used to treat bacterial infections. They do not treat viral infections (e.g., the common cold). When cefuroxime axetil for oral suspension is prescribed to treat a bacterial infection, patients should be told that although it is common to feel better early in the course of therapy, the medication should be taken exactly as directed. Skipping doses or not completing the full course of therapy may: (1) decrease the effectiveness of the immediate treatment, and (2) increase the likelihood that bacteria will develop resistance and will not be treatable by cefuroxime axetil for oral suspension or other antibacterial drugs in the future.

Drug/Laboratory Test Interactions

A false-positive reaction for glucose in the urine may occur with copper reduction tests (Benedict's or Fehling's solution or with CLINITEST® tablets), but not with enzyme-based tests for glycosuria (e.g., CLINISTIX®). As a false-negative result may occur in the ferricyanide test, it is recommended that either the glucose oxidase or hexokinase method be used to determine blood/plasma glucose levels in patients receiving cefuroxime axetil. The presence of cefuroxime does not interfere with the assay of serum and urine creatinine by the alkaline picrate method.

Drug/Drug Interactions

Concomitant administration of probenecid with cefuroxime axetil tablets increases the area under the serum concentration versus time curve by 50%. The peak serum cefuroxime concentration after a 1.5 g single dose is greater when taken with 1 g of probenecid (mean = 14.8 mcg/mL) than without probenecid (mean = 12.2 mcg/mL).

Drugs that reduce gastric acidity may result in a lower bioavailability of cefuroxime axetil compared with that of fasting state and tend to cancel the effect of postprandial absorption.

In common with other antibiotics, cefuroxime axetil may affect the gut flora, leading to lower estrogen reabsorption and reduced efficacy of combined oral estrogen/progesterone contraceptives.

Carcinogenesis, Mutagenesis, and Impairment of Fertility

Although lifetime studies in animals have not been performed to evaluate carcinogenic potential, no mutagenic activity was found for cefuroxime axetil in a battery of bacterial mutation tests. Positive results were obtained in an in vitro chromosome aberration assay, however, negative results were found in an in vivo micronucleus test at doses up to 1.5 g/kg. Reproduction studies in rats at doses up to 1,000 mg/kg/day (9 times the recommended maximum human dose based on mg/m^2) have revealed no impairment of fertility.

Pregnancy

Teratogenic Effects: Pregnancy Category B. Reproduction studies have been performed in mice at doses up to 3,200 mg/kg/day (14 times the recommended maximum human dose based on mg/m^2) and in rats at doses up to 1,000 mg/kg/day (9 times the recommended maximum human dose based on mg/m^2) and have revealed no evidence of impaired fertility or harm to the fetus due to cefuroxime axetil. There are, however, no adequate and well-controlled studies in pregnant women. Because animal reproduction studies are not always predictive of human response, this drug should be used during pregnancy only if clearly needed.

Labor and Delivery

Cefuroxime axetil has not been studied for use during labor and delivery.

Nursing Mothers

Because cefuroxime is excreted in human milk, consideration should be given to discontinuing nursing temporarily during treatment with cefuroxime axetil.

Pediatric Use

The safety and effectiveness of cefuroxime axetil have been established for pediatric patients aged 3 months to 12 years for acute bacterial maxillary sinusitis based upon its approval in adults. Use of cefuroxime axetil in pediatric patients is supported by pharmacokinetic and safety data in adults and pediatric patients, and by clinical and microbiological data from adequate and well-controlled studies of the treatment of acute bacterial maxillary sinusitis in adults and of acute otitis media with effusion in pediatric patients. It is also supported by postmarketing adverse events surveillance (see CLINICAL PHARMACOLOGY, INDICATIONS AND USAGE, ADVERSE REACTIONS, DOSAGE AND ADMINISTRATION, and CLINICAL STUDIES).

Geriatric Use

Of the total number of subjects who received cefuroxime axetil in 20 clinical studies of cefuroxime axetil, 375 were 65 and over while 151 were 75 and over. No overall differences in safety or effectiveness were observed between these subjects and younger adult subjects. The geriatric patients reported somewhat fewer gastrointestinal events and less frequent vaginal candidiasis compared with patients aged 12 to 64 years old; however, no clinically significant differences were reported between the elderly and younger adult patients. Other reported clinical experience has not identified differences in responses between the elderly and younger adult patients.

ADVERSE REACTIONS

In clinical trials using multiple doses of cefuroxime axetil powder for oral suspension, pediatric patients (96.7% of whom were younger than 12 years of age) were treated with the recommended dosages of cefuroxime axetil (20 to 30 mg/kg/day divided twice a day up to a maximum dose of 500 or 1,000 mg/day, respectively). There were no deaths or permanent disabilities in any of the patients in these studies. Eleven U.S. patients (1.2%) discontinued medication due to adverse events thought by the investigators to be possibly, probably, or almost certainly related to drug toxicity. The discontinuations were primarily for gastrointestinal disturbances, usually diarrhea or vomiting. During clinical trials, discontinuation of therapy due to the taste and/or problems with administering this drug occurred in 13 (1.4%) pediatric patients enrolled at centers in the United States.

The following adverse events were thought by the investigators to be possibly, probably, or almost certainly related to cefuroxime axetil for oral suspension in multiple-dose clinical trials (n = 931 cefuroxime axetil-treated U.S. patients).

Table 3: Adverse Reactions—Cefuroxime Axetil For Oral Suspension Multiple-Dose Dosing Regimens—Clinical Trials
Incidence ≥ 1% | Diarrhea/loose stools | 8.6%
 | Dislike of taste | 5 %
 | Diaper rash | 3.4%
 | Nausea/vomiting | 2.6%
Incidence < 1% but > 0.1% | Abdominal pain
 | Flatulence
 | Gastrointestinal infection
 | Candidiasis
 | Vaginal irritation
 | Rash
 | Hyperactivity
 | Irritable behavior
 | Eosinophilia
 | Positive direct Coombs’ test
 | Elevated liver enzymes
 | Viral illness
 | Upper respiratory infection
 | Sinusitis
 | Cough
 | Urinary tract infection
 | Joint swelling
 | Arthralgia
 | Fever
 | Ptyalism

POSTMARKETING EXPERIENCE WITH CEFUROXIME AXETIL PRODUCTS

In addition to adverse events reported during clinical trials, the following events have been identified during clinical practice in patients treated with cefuroxime tablets or with cefuroxime axetil for oral suspension and were reported spontaneously. Data are generally insufficient to allow an estimate of incidence or to establish causation.

General:The following hypersensitivity reactions have been reported: anaphylaxis, angioedema, pruritis, rash, serum sickness-like reaction, and urticaria.

Gastrointestinal: Pseudomembranous colitis (see WARNINGS).

Hematologic: Hemolytic anemia, leukopenia, pancytopenia, thrombocytopenia, and increased prothrombin time.

Hepatic: Hepatic impairment including hepatitis and cholestasis, jaundice.

Neurologic: Seizure.

Skin:Erythema multiforme, Stevens-Johnson syndrome, toxic epidermal necrolysis.

Urologic: Renal dysfunction.

CEPHALOSPORIN-CLASS ADVERSE REACTIONS

In addition to the adverse reactions listed above that have been observed in patients treated with cefuroxime axetil, the following adverse reactions and altered laboratory tests have been reported for cephalosporin-class antibiotics: toxic nephropathy, aplastic anemia, hemorrhage, increased BUN, increased creatinine, false-positive test for urinary glucose, increased alkaline phosphatase, neutropenia, elevated bilirubin, and agranulocytosis.

Several cephalosporins have been implicated in triggering seizures, particularly in patients with renal impairment when the dosage was not reduced (see DOSAGE AND ADMINISTRATION and OVERDOSAGE). If seizures associated with drug therapy occur, the drug should be discontinued. Anticonvulsant therapy can be given if clinically indicated.

OVERDOSAGE

Overdosage of cephalosporins can cause cerebral irritation leading to convulsions. Serum levels of cefuroxime can be reduced by hemodialysis and peritoneal dialysis.

DOSAGE AND ADMINISTRATION

NOTE: CEFUROXIME AXETIL TABLETS AND CEFUROXIME AXETIL FOR ORAL SUSPENSION ARE NOT BIOEQUIVALENT AND ARE NOT SUBSTITUTABLE ON A MILLIGRAM-PER-MILLIGRAM BASIS (SEE CLINICAL PHARMACOLOGY).

Cefuroxime axetil for oral suspension may be administered to pediatric patients ranging in age from 3 months to 12 years, according to dosages in Table 4:

Table 4: Cefuroxime Axetil For Oral Suspension(Must be administered with food. Shake well each time before using.)
Population/Infection | Dosage | Daily Maximum Dose | Duration (days)
Pediatric Patients (3 months to 12 years)
Pharyngitis/tonsillitis | 20 mg/kg/day divided b.i.d. | 500 mg | 10
Acute otitis media | 30 mg/kg/day divided b.i.d. | 1,000 mg | 10
Acute bacterial maxillary sinusitis | 30 mg/kg/day divided b.i.d. | 1,000 mg | 10
Impetigo | 30 mg/kg/day divided b.i.d. | 1,000 mg | 10

Patients With Renal Failure: The safety and efficacy of cefuroxime axetil in patients with renal failure have not been established. Since cefuroxime is renally eliminated, its half-life will be prolonged in patients with renal failure.

Directions for Mixing Cefuroxime Axetil For Oral Suspension: Prepare a suspension at the time of dispensing as follows:

1. Shake the bottle to loosen the powder.

2. Remove the cap.

3. Add the total amount of water for reconstitution (see Table 5) and replace the cap.

4. Vigorously shake in a diagonal direction to form suspension.

Table 5: Amount of Water Required for Reconstitution of Labeled Volumes of Cefuroxime Axetil For Oral Suspension
Cefuroxime Axetil for Oral Suspension | Labeled Volume After Reconstitution | Amount of Water Required for Reconstitution
125 mg/5 mL | 50 mL | 23 mL
125 mg/5 mL | 100 mL | 44 mL
250 mg/5 mL | 50 mL | 22 mL
250 mg/5 mL | 100 mL | 43 mL

NOTE: SHAKE THE ORAL SUSPENSION WELL BEFORE EACH USE. Replace cap securely after each opening. Store the reconstituted suspension between 2 and 8°C (36 and 46°F) (in the refrigerator). DISCARD AFTER 10 DAYS.

HOW SUPPLIED

Cefuroxime Axetil For Oral Suspension USP: When reconstituted as directed, cefuroxime axetil for oral suspension USP provides the equivalent of 125 mg or 250 mg of cefuroxime (as cefuroxime axetil) per 5 mL of suspension. It is supplied as follows:

The 125 mg/5 mL: is a white to cream colored granular powder forming white to cream colored suspension on constitution with water. The resulting suspension has a fruity flavor.

NDC 63304-963-03 50 mL bottles

NDC 63304-963-04 100 mL bottles

The 250 mg/5 mL: is a white to cream colored granular powder forming white to cream colored suspension on constitution with water. The resulting suspension has a fruity flavor.

NDC 63304-964-03 50 mL bottles

NDC 63304-964-04 100 mL bottles

Before reconstitution, store dry powder between 20 - 25° C (68 - 77° F). (See USP Controlled Room Temperature)

After reconstitution, immediately store suspension between 2 - 8° C (36 - 46° F), in a refrigerator. DISCARD AFTER 10 DAYS.

CLINICAL STUDIES

Cefuroxime Axetil Tablets: Acute Bacterial Maxillary Sinusitis: One adequate and well-controlled study was performed in patients with acute bacterial maxillary sinusitis. In this study each patient had a maxillary sinus aspirate collected by sinus puncture before treatment was initiated for presumptive acute bacterial sinusitis. All patients had to have radiographic and clinical evidence of acute maxillary sinusitis. As shown in the following summary of the study, the general clinical effectiveness of cefuroxime axetil tablets was comparable to an oral antimicrobial agent that contained a specific beta-lactamase inhibitor in treating acute maxillary sinusitis. However, sufficient microbiology data were obtained to demonstrate the effectiveness of cefuroxime axetil tablets in treating acute bacterial maxillary sinusitis due only to Streptococcus pneumoniae or non-beta-lactamase-producing Haemophilus influenzae. An insufficient number of beta-lactamase- producing Haemophilus influenzae and Moraxella catarrhalis isolates were obtained in this trial to adequately evaluate the effectiveness of cefuroxime axetil tablets in the treatment of acute bacterial maxillary sinusitis due to these 2 organisms.

This study enrolled 317 adult patients, 132 patients in the United States and 185 patients in South America. Patients were randomized in a 1:1 ratio to cefuroxime axetil 250 mg twice daily or an oral antimicrobial agent that contained a specific beta-lactamase inhibitor. An intent-to-treat analysis of the submitted clinical data yielded the following results:

Table 6: Clinical Effectiveness of Cefuroxime Axetil Tablets Compared to Beta-Lactamase Inhibitor-Containing Control Drug in the Treatment of Acute Bacterial Maxillary Sinusitis
 | U.S. Patients* |  | South American Patients†
 | Cefuroxime Axetil (n = 49) | Control (n = 43) | Cefuroxime Axetil (n = 87) | Control (n = 89)
Clinical success (cure + improvement) | 65% | 53% | 77% | 74%
Clinical cure | 53% | 44% | 72% | 64%
Clinical improvement | 12% | 9% | 5% | 10%

* 95% Confidence interval around the success difference [-0.08, +0.32].

† 95% Confidence interval around the success difference [-0.10, +0.16].

In this trial and in a supporting maxillary puncture trial, 15 evaluable patients had non-beta-lactamase-producing Haemophilus influenzae as the identified pathogen. Ten (10) of these 15 patients (67%) had their pathogen (non-beta-lactamase-producing Haemophilus influenzae) eradicated. Eighteen (18) evaluable patients had Streptococcus pneumoniae as the identified pathogen. Fifteen (15) of these 18 patients (83%) had their pathogen (Streptococcus pneumoniae) eradicated.

Safety: The incidence of drug-related gastrointestinal adverse events was statistically significantly higher in the control arm (an oral antimicrobial agent that contained a specific beta-lactamase inhibitor) versus the cefuroxime axetil arm (12% versus 1%, respectively; P < .001), particularly drug-related diarrhea (8% versus 1%, respectively; P = .001).

Early Lyme Disease: Two adequate and well-controlled studies were performed in patients with early Lyme disease. In these studies all patients had to present with physician-documented erythema migrans, with or without systemic manifestations of infection. Patients were randomized in a 1:1 ratio to a 20-day course of treatment with cefuroxime axetil 500 mg twice daily or doxycycline 100 mg 3 times daily. Patients were assessed at 1 month posttreatment for success in treating early Lyme disease (Part I) and at 1 year posttreatment for success in preventing the progression to the sequelae of late Lyme disease (Part II).

A total of 355 adult patients (181 treated with cefuroxime axetil and 174 treated with doxycycline) were enrolled in the 2 studies. In order to objectively validate the clinical diagnosis of early Lyme disease in these patients, 2 approaches were used: 1) blinded expert reading of photographs, when available, of the pretreatment erythema migrans skin lesion; and 2) serologic confirmation (using enzyme-linked immunosorbent assay [ELISA] and immunoblot assay [“Western” blot]) of the presence of antibodies specific to Borrelia burgdorferi, the etiologic agent of Lyme disease. By these procedures, it was possible to confirm the physician diagnosis of early Lyme disease in 281 (79%) of the 355 study patients. The efficacy data summarized below are specific to this “validated” patient subset, while the safety data summarized below reflect the entire patient population for the 2 studies.

Analysis of the submitted clinical data for evaluable patients in the “validated” patient subset yielded the following results:

Table 7: Clinical Effectiveness of Cefuroxime Axetil Tablets Compared to Doxycycline in the Treatment of Early Lyme Disease
 | Part I (1 Month Posttreatment)* |  | Part II (1 Year Posttreatment)†
 | Cefuroxime Axetil | Doxycycline | Cefuroxime Axetil | Doxycycline
 | (n = 125) | (n = 108) | (n = 105‡) | (n = 83‡)
Satisfactory clinical outcome§ | 91% | 93% | 84% | 87%
Clinical cure/success | 72% | 73% | 73% | 73%
Clinical improvement | 19% | 19% | 10% | 13%

* 95% confidence interval around the satisfactory difference for Part I (-0.08, +0.05).

† 95% confidence interval around the satisfactory difference for Part II (-0.13, +0.07).

‡ n’s include patients assessed as unsatisfactory clinical outcomes (failure + recurrence) in Part I (cefuroxime axetil - 11 [5 failure, 6 recurrence]; doxycycline - 8 [6 failure, 2 recurrence]).

§ Satisfactory clinical outcome includes cure + improvement (Part I) and success + improvement (Part II).

Cefuroxime axetil and doxycycline were effective in prevention of the development of sequelae of late Lyme disease.

Safety: Drug-related adverse events affecting the skin were reported significantly more frequently by patients treated with doxycycline than by patients treated with cefuroxime axetil (12% versus 3%, respectively; P = .002), primarily reflecting the statistically significantly higher incidence of drug-related photosensitivity reactions in the doxycycline arm versus the cefuroxime axetil arm (9% versus 0%, respectively; P < .001). While the incidence of drug-related gastrointestinal adverse events was similar in the 2 treatment groups (cefuroxime axetil - 13%; doxycycline - 11%), the incidence of drug-related diarrhea was statistically significantly higher in the cefuroxime axetil arm versus the doxycycline arm (11% versus 3%, respectively; P = .005).

Secondary Bacterial Infections of Acute Bronchitis: Four randomized, controlled clinical studies were performed comparing 5 days versus 10 days of cefuroxime axetil for the treatment of patients with secondary bacterial infections of acute bronchitis. These studies enrolled a total of 1,253 patients (CAE-516 n = 360; CAE-517 n = 177; CAEA4001 n = 362; CAEA4002 n = 354). The protocols for CAE-516 and CAE-517 were identical and compared cefuroxime axetil 250 mg twice daily for 5 days, cefuroxime axetil 250 mg twice daily for 10 days, and AUGMENTIN® 500 mg 3 times daily for 10 days. These 2 studies were conducted simultaneously. CAEA4001 and CAEA4002 compared cefuroxime axetil 250 mg twice daily for 5 days, cefuroxime axetil 250 mg twice daily for 10 days, and CECLOR® 250 mg 3 times daily for 10 days. They were otherwise identical to CAE-516 and CAE-517 and were conducted over the following 2 years. Patients were required to have polymorphonuclear cells present on the Gram stain of their screening sputum specimen, but isolation of a bacterial pathogen from the sputum culture was not required for inclusion. The following table demonstrates the results of the clinical outcome analysis of the pooled studies CAE-516/CAE-517 and CAEA4001/CAEA4002, respectively:

Table 8: Clinical Effectiveness of Cefuroxime Axetil Tablets 250 mg Twice Daily in Secondary Bacterial Infections of Acute Bronchitis: Comparison of 5 Versus 10 Days’ Treatment Duration
 | CAE-516 and CAE-517* |  | CAEA4001 and CAEA4002†
 | 5 Day (n = 127) | 10 Day (n = 139) | 5 Day (n = 173) | 10 Day (n = 192)
Clinical success (cure + improvement) | 80% | 87% | 84% | 82%
Clinical cure | 61% | 70% | 73% | 72%
Clinical improvement | 19% | 17% | 11% | 10%

* 95% Confidence interval around the success difference [-0.164, +0.029].

† 95% Confidence interval around the success difference [-0.061, +0.103].

The response rates for patients who were both clinically and bacteriologically evaluable were consistent with those reported for the clinically evaluable patients.

Safety: In these clinical trials, 399 patients were treated with cefuroxime axetil for 5 days and 402 patients with cefuroxime axetil for 10 days. No difference in the occurrence of adverse events was observed between the 2 regimens.

REFERENCES

1. National Committee for Clinical Laboratory Standards. Methods for Dilution Antimicrobial Susceptibility Tests for Bacteria that Grow Aerobically. 3rd ed. Approved Standard NCCLS Document M7-A3, Vol. 13, No. 25. Villanova, Pa: NCCLS; 1993.

2. National Committee for Clinical Laboratory Standards. Performance Standards for Antimicrobial Disk Susceptibility Tests. 4th ed. Approved Standard NCCLS Document M2-A4, Vol. 10, No. 7. Villanova, Pa: NCCLS; 1990.

CLINITEST and CLINISTIX are registered trademarks of Ames Division, Miles Laboratories, Inc.

CECLOR® is a registered trademark of Lilly.

AUGMENTIN® is a registered trademark of GlaxoSmithKline

Manufactured for:

Ranbaxy Pharmaceuticals Inc.

Jacksonville, FL 32257 USA

by: Ranbaxy Laboratories Limited

New Delhi - 110 019, India

September 2007

PACKAGE LABEL. PRINCIPAL DISPLAY PANEL.

RANBAXY

NDC 63304-963-04

CEFUROXIME AXETIL FOR ORAL SUSPENSION, USP

Rx only 100 ml

125 mg-5 ml bottle label

RANBAXY

NDC 63304-964-03

CEFUROXIME AXETIL FOR ORAL SUSPENSION, USP

Rx only 50 ml

250 mg-5 ml bottle label